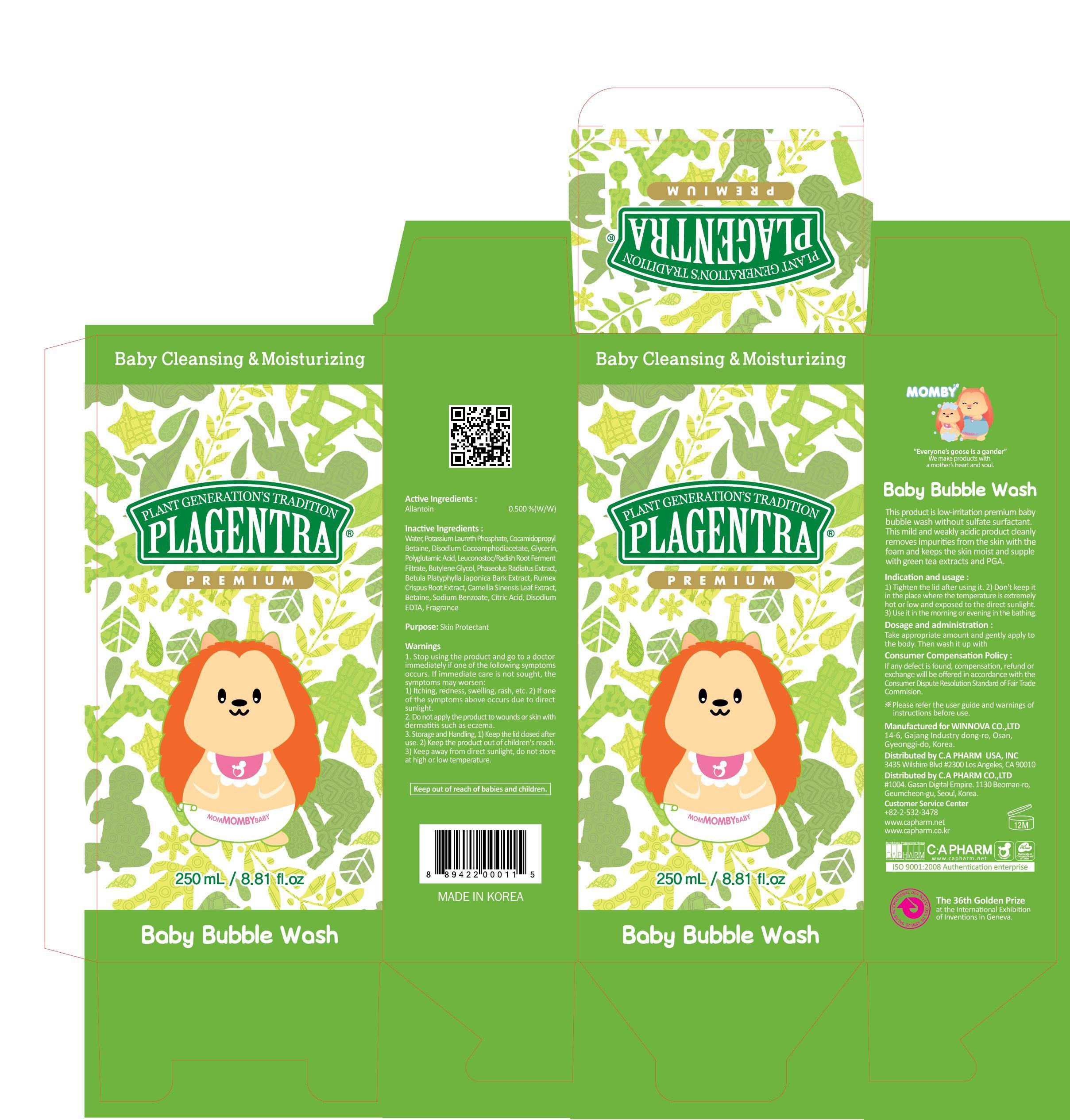 DRUG LABEL: PLAGENTRA BABY BUBBLE WASH
NDC: 68988-080 | Form: AEROSOL, FOAM
Manufacturer: C.A Pharm Co., Ltd.
Category: otc | Type: HUMAN OTC DRUG LABEL
Date: 20141208

ACTIVE INGREDIENTS: Allantoin 1.25 mg/250 mL
INACTIVE INGREDIENTS: Water; Glycerin

ACTIVE INGREDIENT

Active Ingredient: Allantoin 0.5%

INACTIVE INGREDIENT

Inactive Ingredients:
Water, Potassium Laureth Phosphate, Cocamidopropyl Betaine, Disodium Cocoamphodiacetate, Glycerin, Polyglutamic Acid, Leuconostoc/Radish Root Ferment Filtrate, Butylene Glycol, Phaseolus Radiatus Extract, Betula Platyphylla Japonica Bark Extract, Rumex Crispus Root Extract, Camellia Sinensis Leaf Extract, Betaine, Sodium Benzoate, Citric Acid, Disodium EDTA, Fragrance

PURPOSE

Purpose: Skin Portectant

WARNINGS

1. Stop using the product and go to a doctor immediately if one of the following symptoms occurs. If immediate care is not sought, the symptoms may worsen :
1) Itching, redness, swelling, rash, etc. 2) If one of the symptoms above occurs due to direct sunlight.
2. Do not apply the product to wounds or skin with dermatitis such as eczema.
3. Storage and Handling, 1) Keep the lid closed after use. 2) Keep the product out of children's reach. 3) Keep away from direct sunlight, do not store at high or low temperature.

KEEP OUT OF REACH OF CHILDREN

Keep out of reach of babies and children.

INDICATIONS & USAGE

Indication and usage:
1) Tighten the lid after using it.
2) Don't keep it in the place where the temperature is extremely hot or low and exposed to the direct sunlight.
3) Use it in the morning or evening in the bath.

DOSAGE & ADMINISTRATION

Dosage and administration:
Take appropriate amount and gently apply to the body.
Then wash it up with.